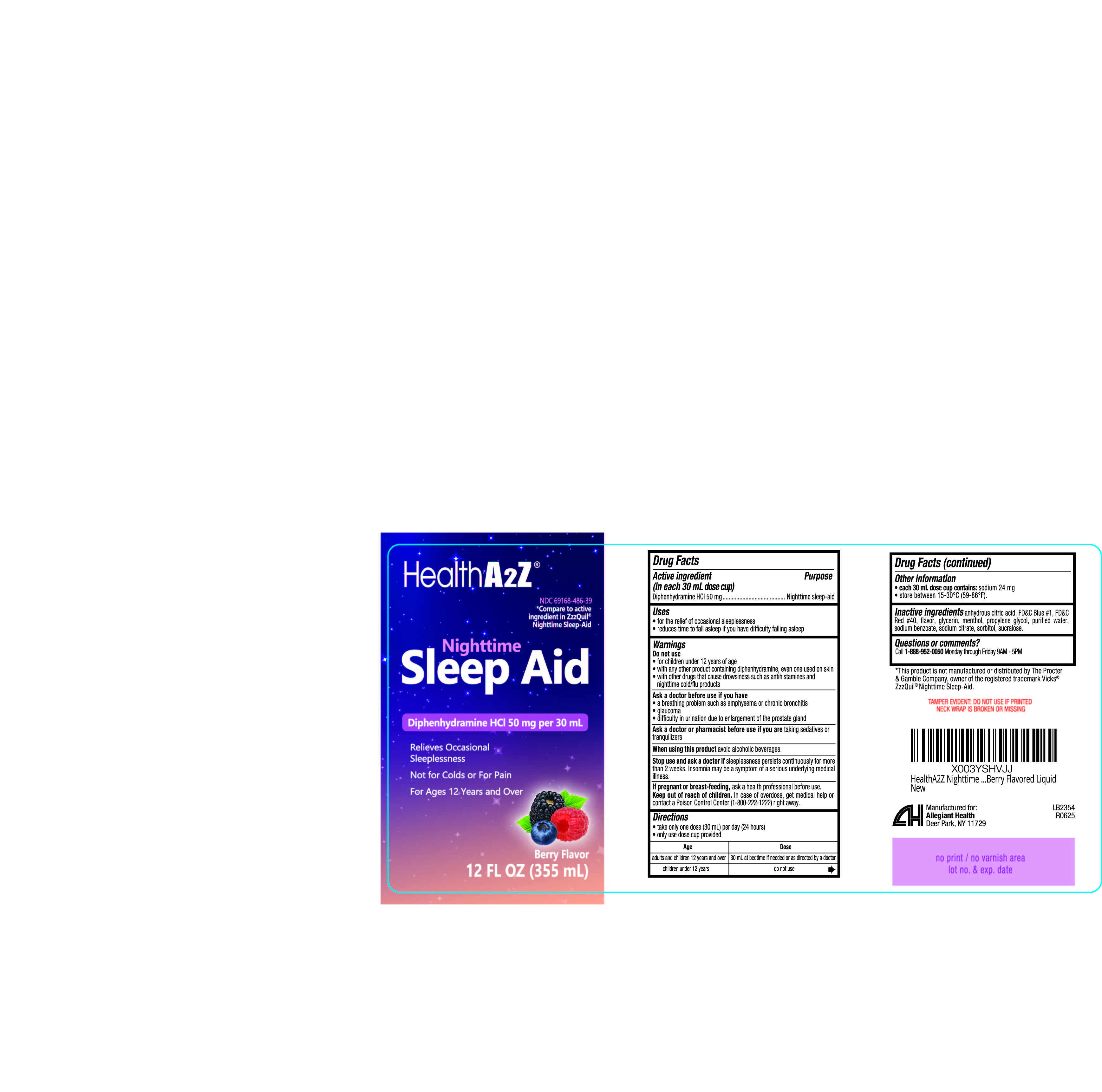 DRUG LABEL: Nighttime Sleep Aid
NDC: 69168-486 | Form: LIQUID
Manufacturer: Allegiant Health
Category: otc | Type: HUMAN OTC DRUG LABEL
Date: 20250806

ACTIVE INGREDIENTS: DIPHENHYDRAMINE HYDROCHLORIDE 50 mg/30 mL
INACTIVE INGREDIENTS: ANHYDROUS CITRIC ACID; FD&C BLUE NO. 1; FD&C RED NO. 40; GLYCERIN; MENTHOL; PROPYLENE GLYCOL; WATER; SODIUM BENZOATE; SODIUM CITRATE; SORBITOL; SUCRALOSE

486 - Nighttime Sleep Aid

Active ingredient(s)

Diphenhydramine HCl 50 mg (in each 30 mL)

Purpose

Nighttime sleep-aid

Use(s)

- for the relief of occasional sleeplessness
- reduces time to fall asleep if you have difficulty falling asleep

Warnings

Do not use

- for children under 12 years of age
- with any other product containing diphenhydramine, even one used on skin
- with other drugs that cause drowsiness such as antihistamines and nighttime cold/flu product

Ask a doctor before use if you

have
• a breathing problem such as emphysema or chronic bronchitis
• glaucoma
• difficulty in urination due to enlargement of the prostate gland

Ask a doctor or pharmacist before use if

if you are taking sedatives or tranquilizers

When using this product

avoid alcoholic beverages.

Stop use and ask a doctor if

sleeplessness persists continuously for more
than 2 weeks. Insomnia may be a symptom of a serious underlying medical
illness.

If pregnant or breastfeeding,

ask a health professional before use.

Keep out of reach of children

In case of overdose, get medical help or contact a Poison Control Center (1-800-222-1222) right away.

Directions

• take only one dose (30 mL) per day (24 hours)
• only use dose cup provided

Age | Dose
adults & children 12 yrs & over | 30 mL at bedtime if needed or as directed by a doctor
children under 12 yrs | do not use

Other information

• each 30 mL dose cup contains: sodium 24 mg
• store between 15-30°C (59-86°F).

TAMPER EVIDENT: DO NOT USE IF PRINTED NECK WRAP IS BROKEN OR MISSING

Inactive ingredients

anhydrous citric acid, FD&C Blue #1, FD&C
Red #40, flavor, glycerin, menthol, propylene glycol, purified water,
sodium benzoate, sodium citrate, sorbitol, sucralose.

Questions/Comments

Call 1-888-952-0050

(Monday-Friday 9 AM – 5 PM EST)

Principal Display Panel

Nighttime Sleep Aid